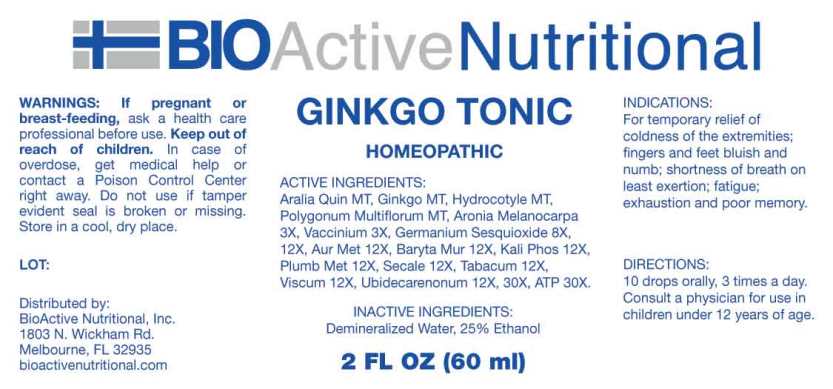 DRUG LABEL: Ginkgo Tonic
NDC: 43857-0383 | Form: LIQUID
Manufacturer: BioActive Nutritional, Inc.
Category: homeopathic | Type: HUMAN OTC DRUG LABEL
Date: 20241017

ACTIVE INGREDIENTS: AMERICAN GINSENG 1 [hp_X]/1 mL; GINKGO 1 [hp_X]/1 mL; CENTELLA ASIATICA WHOLE 1 [hp_X]/1 mL; FALLOPIA MULTIFLORA ROOT 1 [hp_X]/1 mL; ARONIA MELANOCARPA FRUIT 3 [hp_X]/1 mL; BILBERRY 3 [hp_X]/1 mL; GERMANIUM SESQUIOXIDE 8 [hp_X]/1 mL; GOLD 12 [hp_X]/1 mL; BARIUM CHLORIDE DIHYDRATE 12 [hp_X]/1 mL; POTASSIUM PHOSPHATE, DIBASIC 12 [hp_X]/1 mL; LEAD 12 [hp_X]/1 mL; CLAVICEPS PURPUREA SCLEROTIUM 12 [hp_X]/1 mL; TOBACCO LEAF 12 [hp_X]/1 mL; VISCUM ALBUM FRUITING TOP 12 [hp_X]/1 mL; UBIDECARENONE 12 [hp_X]/1 mL; ADENOSINE TRIPHOSPHATE DISODIUM 30 [hp_X]/1 mL
INACTIVE INGREDIENTS: WATER; ALCOHOL

DRUG FACTS:

ACTIVE INGREDIENTS:

Aralia Quinquefolia MT, Ginkgo Biloba MT, Hydrocotyle Asiatica MT, Polygonum Multiflorum MT, Aronia Melanocarpa 3X, Vaccinium Myrtillus 3X, Germanium Sesquioxide 8X, 12X, Aurum Metallicum 12X, Baryta Muriatica 12X, Kali Phosphoricum 12X, Plumbum Metallicum 12X, Secale Cornutum 12X, Tabacum 12X, Viscum Album 12X, Ubidecarenonum 12X, 30X, Adenosinum Triphosphoricum Dinatrum 30X.

INDICATIONS:

For temporary relief of coldness of the extremities; fingers and feet bluish and numb; shortness of breath on least exertion; fatigue; exhaustion and poor memory.

WARNINGS:

If pregnant or breast-feeding, ask a health care professional before use.

Keep out of reach of children. In case of overdose, get medical help or contact a Poison Control Center right away.

Do not use if tamper evident seal is broken or missing.

Store in cool, dry place.

Keep out of reach of children. In case of overdose, get medical help or contact a Poison Control Center right away.

DIRECTIONS:

10 drops orally, 3 times a day. Consult a physician for use in children under 12 years of age.

INDICATIONS:

For temporary relief of coldness of the extremities; fingers and feet bluish and numb; shortness of breath on least exertion; fatigue; exhaustion and poor memory.

INACTIVE INGREDIENTS:

Demineralized Water, 25% Ethanol.

QUESTIONS:

Distributed by:

BIOACTIVE NUTRITIONAL

Melbourne, FL 32935

For Nutritional Information write:

BioActive Nutritional, Inc.

1803 N. Wickham Rd.

Melbourne, FL 32935

PACKAGE LABEL DISPLAY:

BioActive Homeopathic

GINKGO TONIC

2 FL OZ (60 ml)